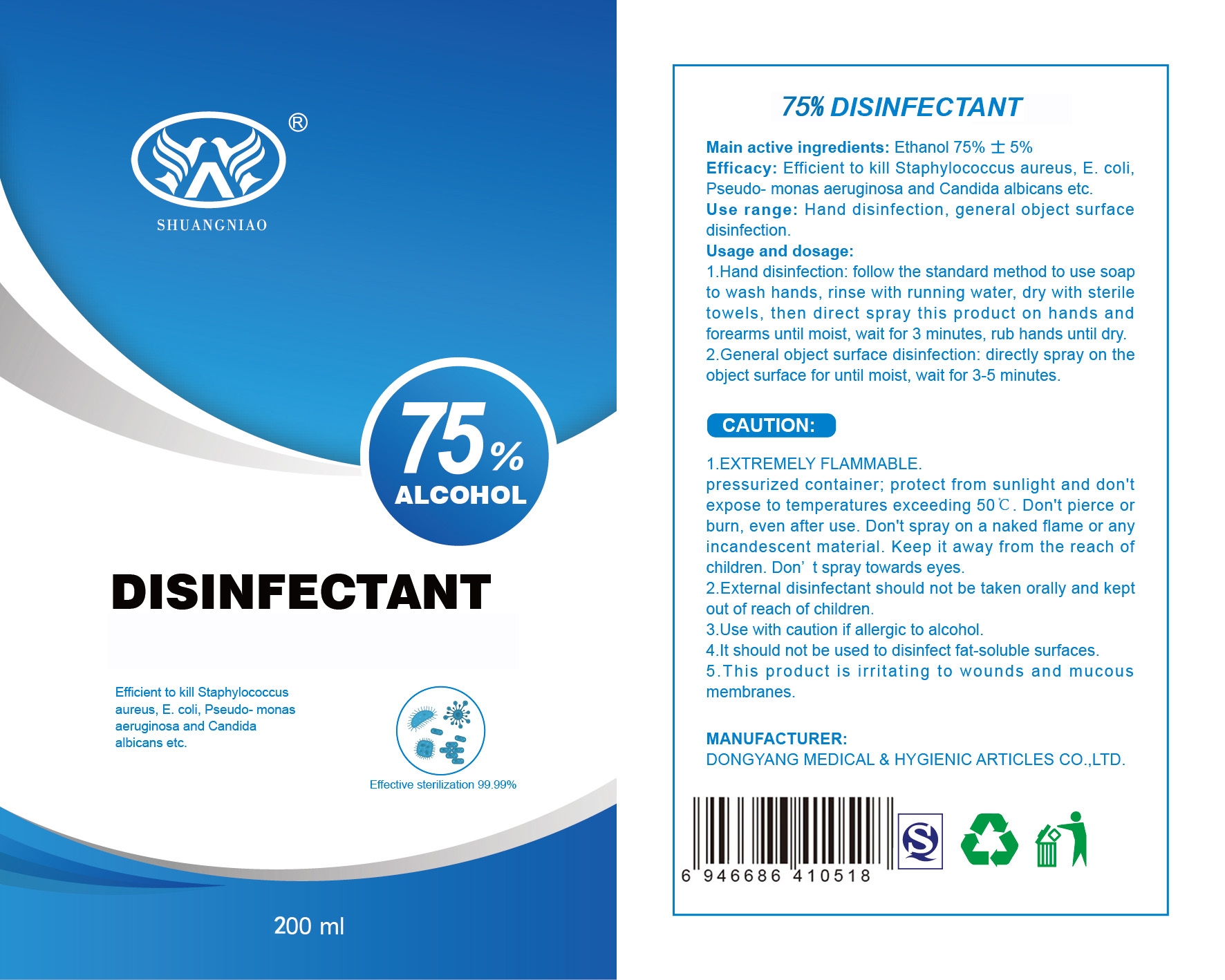 DRUG LABEL: 75% ALCOHOL DISINFECTANT
NDC: 81276-014 | Form: LIQUID
Manufacturer: Dongyang Medical & Hygienic Articles Co., Ltd.
Category: otc | Type: HUMAN OTC DRUG LABEL
Date: 20201227

ACTIVE INGREDIENTS: ALCOHOL 150 mL/200 mL
INACTIVE INGREDIENTS: WATER

81276-014-01 200ml

Active Ingredient(s)

ALCOHOL DENAT. 75%

Purpose

efficient to kill staphylococcus aureus,e. coil, pseudo-monas aeruginosa and candida albicans etc

Use

1.Hand disinfection:follow the standard method to use soap to wash hands,rinse with running water,dry with sterile towels,then direct spray this product on hands and forearms until moist,wait for 3 minutes, rub hands until dry.
2.General object surface disinfection:directly spray on the object surface for until moist,wait for 3-5 minutes.

Warnings

1.EXTREMELY FLAMMABLE.

pressurized container; protect from sunlight and don't expose to temperatures exceeding 50℃ . Don't pierce or burn, even after use. Don't spray on a naked flame or any incandescent material. Keep it away from the reach of children . Don't spray towards eyes.

2.External disinfectant should not be taken orally and kept out of reach of children.

3.Use with caution if allergic to alcohol.

4.It should not be used to disinfect fat-soluble surface.

5.This product is irritating to wounds and mucous membranes.

Do not use

- in children less than 2 months of age
- on open skin wounds

When using this product keep out of eyes, ears, and mouth. In case of contact with eyes, rinse eyes thoroughly with water.
Stop use and ask a doctor if irritation or rash occurs. These may be signs of a serious condition.
Keep out of reach of children. If swallowed, get medical help or contact a Poison Control Center right away.

Stop use and ask a doctor if irritation or rash occurs. These may be signs of a serious condition.

Keep out of reach of children. If swallowed, get medical help or contact a Poison Control Center right away.

Directions

- 1.Hand disinfection:follow the standard method to use soap to wash hands,rinse with running water,dry with sterile towels,then direct spray this product on hands and forearms until moist,wait for 3 minutes, rub hands until dry.
- 2.General object surface disinfection:directly spray on the object surface for until moist,wait for 3-5 minutes.

Other information

- Store between 15-30C (59-86F)
- Avoid freezing and excessive heat above 40C (104F)

Inactive ingredients

Water

Package Label - Principal Display Panel

200 ml in 1 bottle NDC:81276-014-01